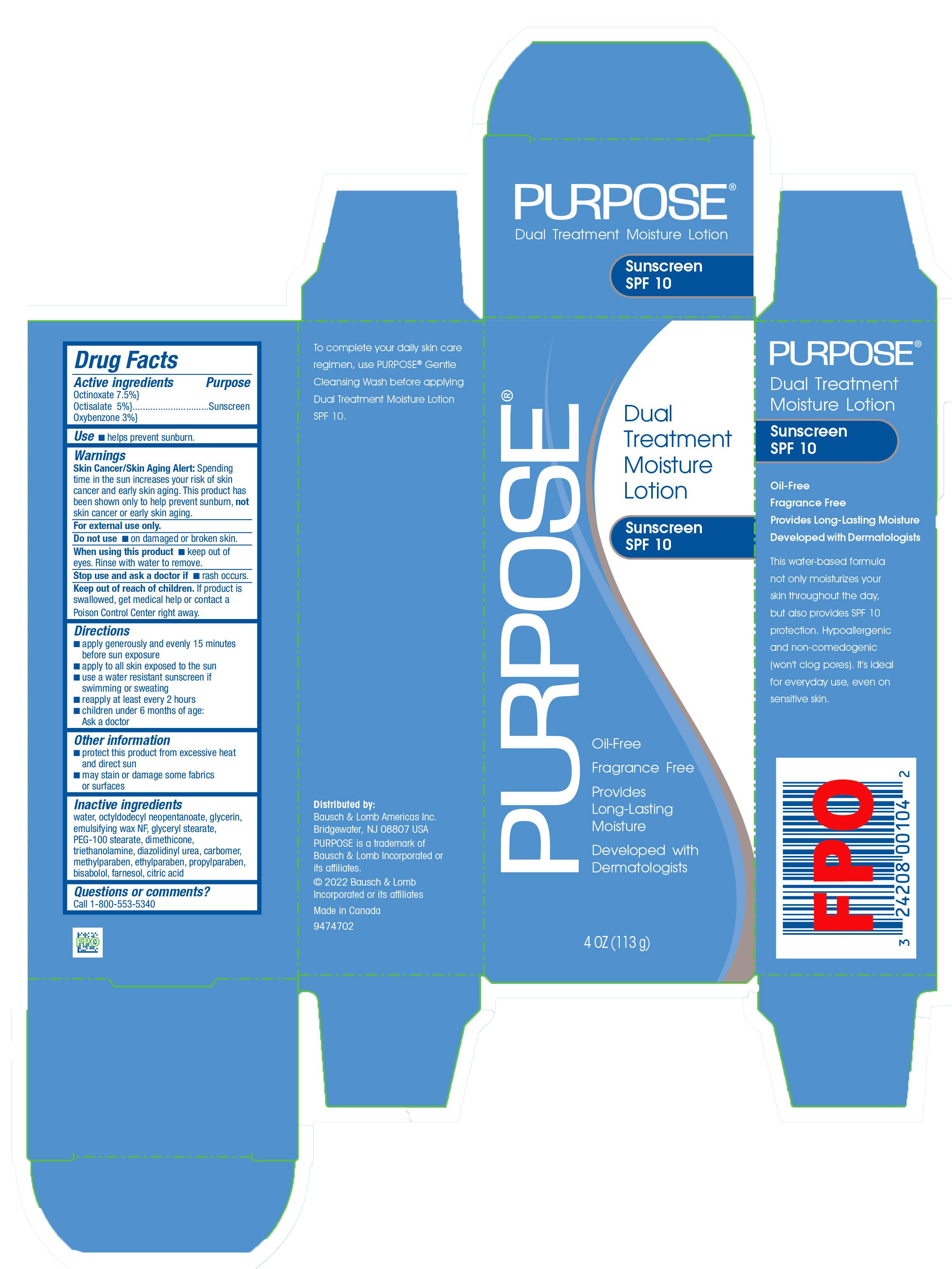 DRUG LABEL: Purpose Dual Treatment SPF 10
NDC: 87033-2000 | Form: LOTION
Manufacturer: Elysium Consumer Healthcare LLC
Category: otc | Type: HUMAN OTC DRUG LABEL
Date: 20250829

ACTIVE INGREDIENTS: OXYBENZONE 3 g/100 g; OCTINOXATE 7.5 g/100 g; OCTISALATE 5 g/100 g
INACTIVE INGREDIENTS: BISABOLOL; GLYCERYL STEARATE SE; OCTYLDODECYL NEOPENTANOATE; SYNTHETIC WAX (1900 MW); PEG-100 STEARATE; TRIETHANOLAMINE; PROPYLPARABEN; DIAZOLIDINYL UREA; METHYLPARABEN; CITRIC ACID; FARNESOL; ETHYLPARABEN; GLYCERIN; CARBOMER; DIMETHICONE; WATER

Purpose Dual Treatment Moisture Lotion SPF 10

Active ingredients

Octinoxate 7.5%, Octisalate 5%, Oxybenzone 3%

Purpose

Sunscreen

Uses

helps prevent sunburn

Warnings

Skin Cancer/Skin Aging Alert: Spending time in the sun increases your risk of skin cancer and ealy skin aging. This product has been shown only to help prevent sunburn, not skin cancer or early skin aging.

For external use only

Do not use

on damaged or broken skin

When using this product

keep out of eyes. Rinse with water to remove.

Stop use and ask a doctor if

rash occurs

Keep out of reach of children

if poduct is swallowed, get medical help or contact a Poison Contro Center right away

Directions

- apply generously and evenly 15 minutes before sun exposure
- apply to all skin exposed to the sun
- use a water reistant sunscreen if swimming or sweating
- reapply at least every 2 hours
- children un 6 months of age: Ask a doctor

Other information

- protect this product from excesssive heat and direct sun
- may stain or damge som farics or surfaces

Inactive ingredients

water, octyldodecyl neopentanoate, glycerin, emulsifying wax NF, glyceryl stearate, PEG-100 stearate, dimethicone, triethanolamine, diazolidinyl urea, carbomer, methylparaben, ethylparaben, propylparaben, bisabolol, farnesol, citric acid

Questions or comments?

Call 1-800-553-5340

Purpose

Dual Treatment Mosture Lotion

Sunscreen SPF 10

Oil-Free

Fragrance Free

Provides Long-Lasting Moisture

Developed with Dermatologists